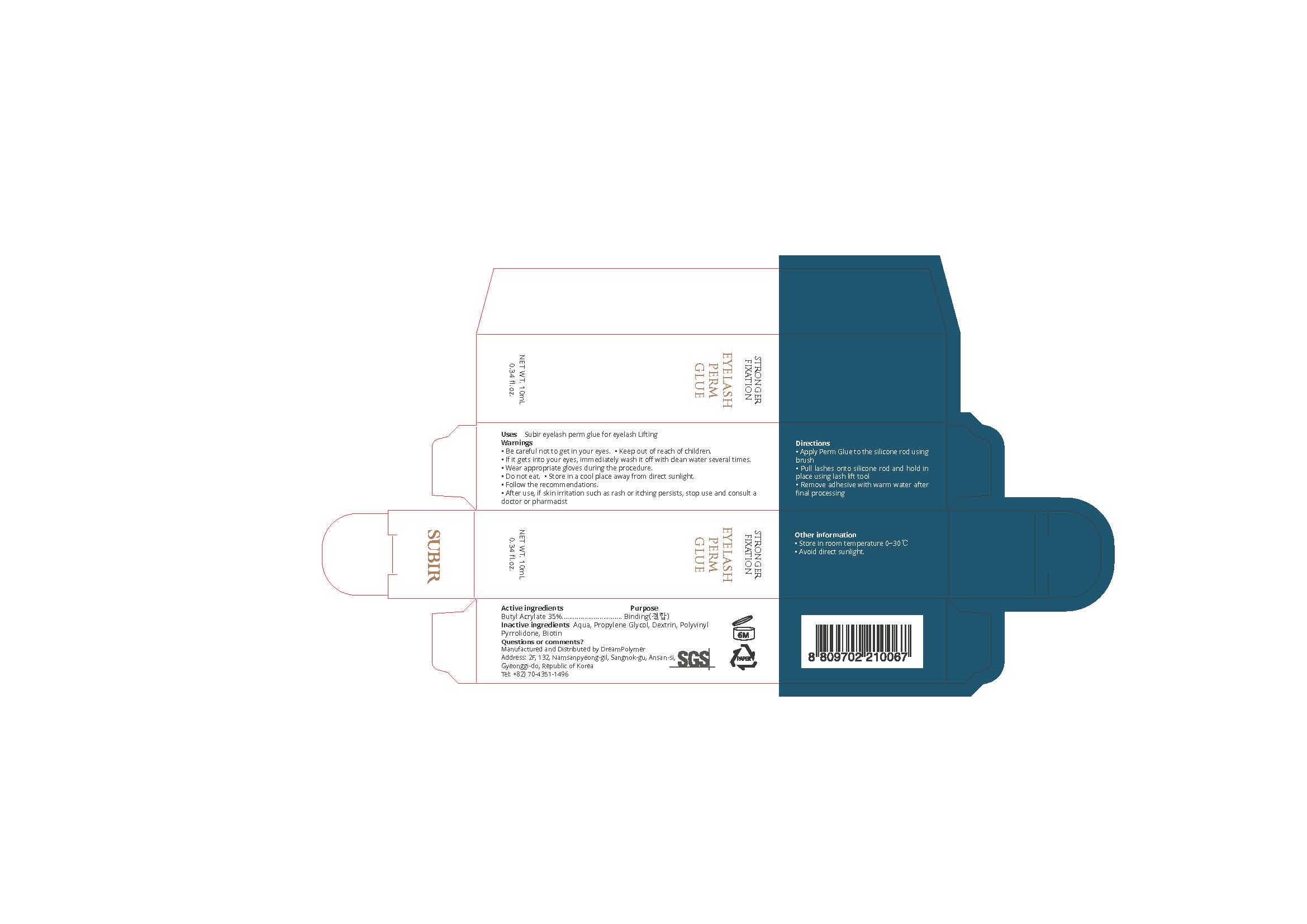 DRUG LABEL: SUBIR EYELASH
NDC: 81716-005 | Form: CREAM
Manufacturer: Dream Polymer
Category: otc | Type: HUMAN OTC DRUG LABEL
Date: 20210330

ACTIVE INGREDIENTS: Butyl Acrylate 3.5 g/10 g
INACTIVE INGREDIENTS: Water; Propylene Glycol; Biotin

Active Ingredient(s)

Butyl Acrylate 35%

Purpose

Binding

Use

Subir eyelash perm glue for eyelash Lifting

Warnings

• Be careful not to get in your eyes. • Keep out of reach of children.
• If it gets into your eyes, immediately wash it off with clean water several times.
• Wear appropriate gloves during the procedure.
• Do not eat. • Store in a cool place away from direct sunlight.
• Follow the recommendations.
• After use, if skin irritation such as rash or itching persists, stop use and consult a doctor or pharmacist

 Keep out of reach of children.

Directions

• Apply Perm Glue to the silicone rod using brush
• Pull lashes onto silicone rod and hold in place using lash lift tool
• Remove adhesive with warm water after final processing

Other information

・ Store in room temperature 0~30℃
・ Avoid direct sunlight.

Inactive ingredients

Aqua, Propylene Glycol, Dextrin, Polyvinyl Pyrrolidone, Biotin